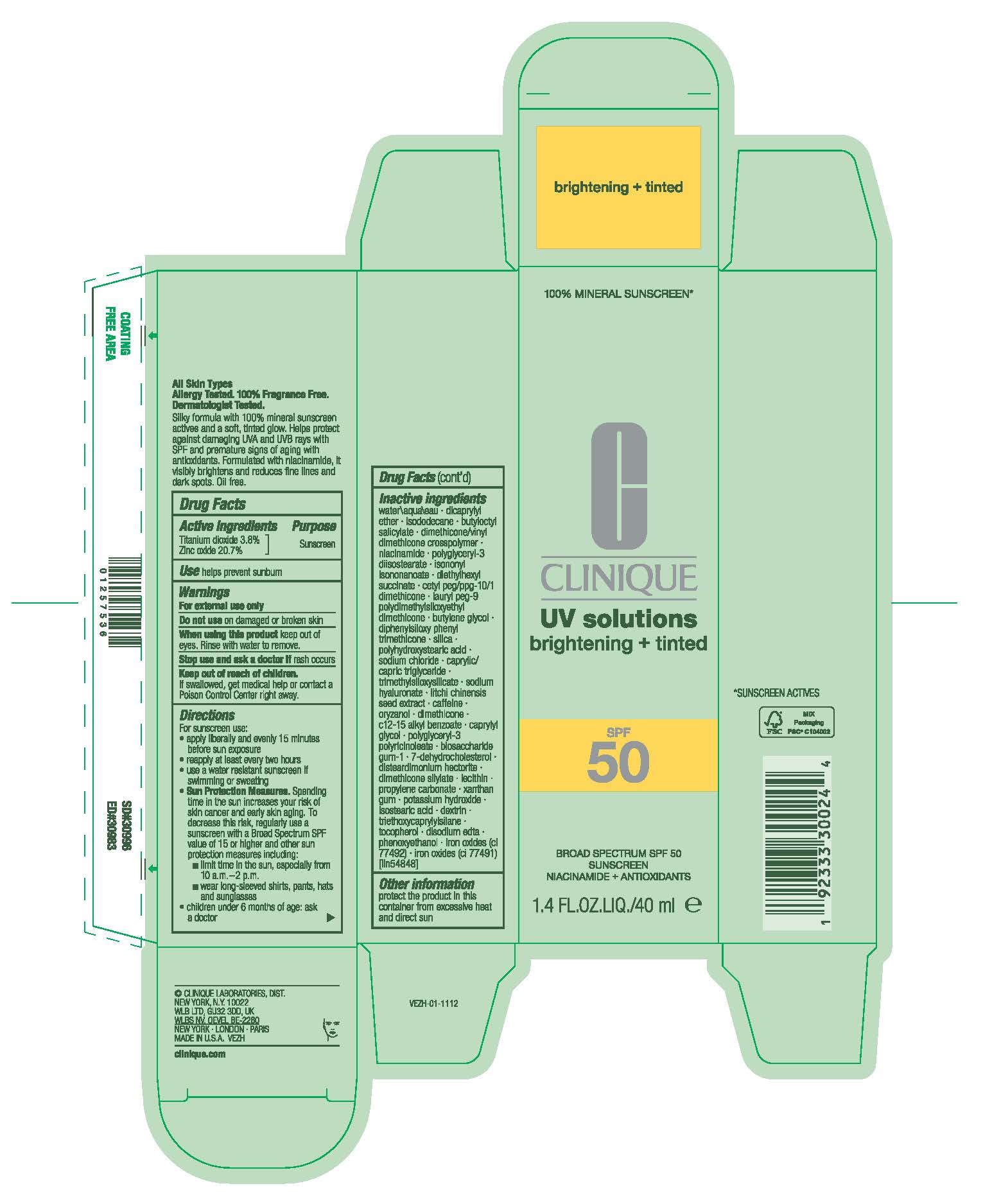 DRUG LABEL: UV SOLUTIONS BRIGHTENING TINTED BROAD SPECTRUM SPF 50 SUNSCREEN NIACINAMIDE ANTIOXIDANTS
NDC: 49527-227 | Form: CREAM
Manufacturer: CLINIQUE LABORATORIES LLC
Category: otc | Type: HUMAN OTC DRUG LABEL
Date: 20250806

ACTIVE INGREDIENTS: ZINC OXIDE 207 mg/1 mL; TITANIUM DIOXIDE 38 mg/1 mL
INACTIVE INGREDIENTS: CETYL PEG/PPG-10/1 DIMETHICONE (HLB 5); XANTHAN GUM; ISOSTEARIC ACID; DIPHENYLSILOXY PHENYL TRIMETHICONE; TRIETHOXYCAPRYLYLSILANE; FERRIC OXIDE RED; SODIUM CHLORIDE; TRIMETHYLSILOXYSILICATE (M/Q 0.6-0.8); ISONONYL ISONONANOATE; 7-DEHYDROCHOLESTEROL; TOCOPHEROL; BIOSACCHARIDE GUM-1; POLYHYDROXYSTEARIC ACID (2300 MW); SODIUM HYALURONATE; ORYZANOL; NIACINAMIDE; DIETHYLHEXYL SUCCINATE; DICAPRYLYL ETHER; BUTYLENE GLYCOL; BUTYLOCTYL SALICYLATE; WATER; DIMETHICONE/VINYL DIMETHICONE CROSSPOLYMER (HARD PARTICLE); POLYGLYCERYL-3 DIISOSTEARATE; CAPRYLIC/CAPRIC TRIGLYCERIDE; C12-15 ALKYL BENZOATE; CAPRYLYL GLYCOL; POTASSIUM HYDROXIDE; ICODEXTRIN; ISODODECANE; LAURYL PEG-9 POLYDIMETHYLSILOXYETHYL DIMETHICONE; EDETATE DISODIUM ANHYDROUS; PHENOXYETHANOL; SILICA; LECITHIN, SOYBEAN; FERRIC OXIDE YELLOW; LITCHI CHINENSIS SEED; CAFFEINE; DIMETHICONE; DISTEARDIMONIUM HECTORITE; PROPYLENE CARBONATE

UV SOLUTIONS BRIGHTENING + TINTED BROAD SPECTRUM SPF 50 SUNSCREEN NIACINAMIDE+ANTIOXIDANTS

Active ingredients

TITANIUM DIOXIDE 3.8%
ZINC OXIDE 20.7%

Purpose

Sunscreen

Use

helps prevent sunburn

Warnings

For external use only

Do not use

on damaged or broken skin

When using this product

keep out of eyes. Rinse with water to remove.

Stop use and ask a doctor if

rash occurs

Keep out of reach of children.

If product is swallowed, get medical help or contact a Poison Control Center right away.

Directions

For sunscreen use:
apply liberally 15 minutes before sun exposure
reapply at least every two hours
use a water resistant sunscreen if swimming or sweating
Sun Protection Measures. Spending time in the sun increases your risk of skin cancer and early skin aging. To decrease this risk, regularly use a sunscreen with a Broad Spectrum SPF value of 15 or higher and other sun protection measures including:
limit time in the sun, especially from 10 a.m.–2 p.m.
wear long-sleeved shirts, pants, hats and sunglasses
children under 6 months of age: ask a doctor

Inactive Ingredients

water\aqua\eau,dicaprylyl ether,isododecane,butyloctyl salicylate,dimethicone/vinyl dimethicone crosspolymer,niacinamide,polyglyceryl-3 diisostearate,isononyl isononanoate,diethylhexyl succinate,cetyl peg/ppg-10/1 dimethicone,lauryl peg-9 polydimethylsiloxyethyl dimethicone,butylene glycol,diphenylsiloxy phenyl trimethicone,silica,polyhydroxystearic acid,sodium chloride,caprylic/capric triglyceride,trimethylsiloxysilicate,sodium hyaluronate,litchi chinensis seed extract,caffeine,oryzanol,dimethicone,c12-15 alkyl benzoate,caprylyl glycol,polyglyceryl-3 polyricinoleate,biosaccharide gum-1,7-dehydrocholesterol,disteardimonium hectorite,dimethicone silylate,lecithin,propylene carbonate,xanthan gum,potassium hydroxide,isostearic acid,dextrin,triethoxycaprylylsilane,tocopherol,disodium edta,phenoxyethanol,iron oxides (ci 77492),iron oxides (ci 77491) [iln54848]

Other information

protect the product in this container from excessive heat and direct sun

PDP

CLINIQUE
UV solutions
brightening + tinted

BROAD SPECTRUM SPF 50

SUNSCREEN

NIACINAMIDE + ANTIOXIDANTS

1.4 FL. OZ.LIQ/40ml